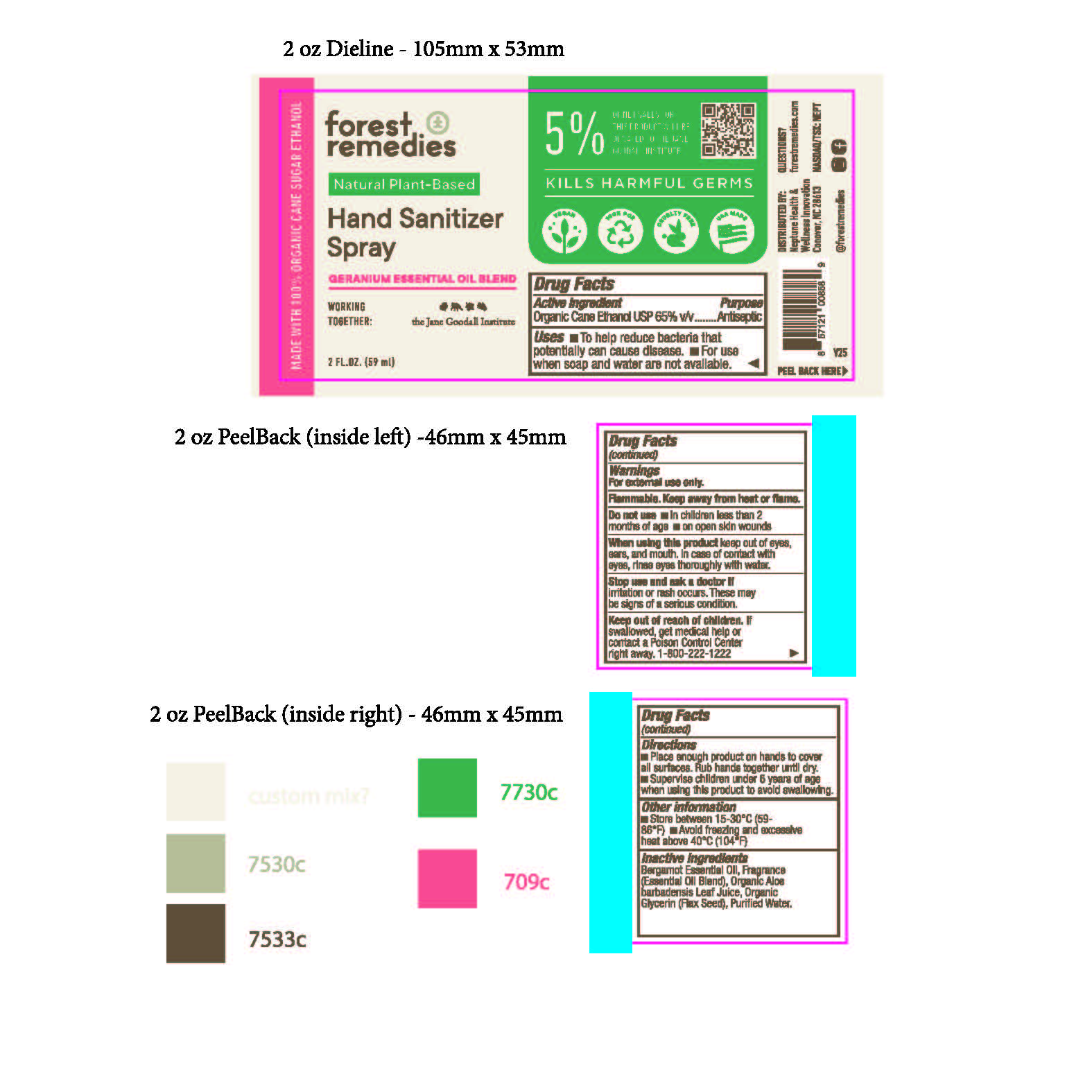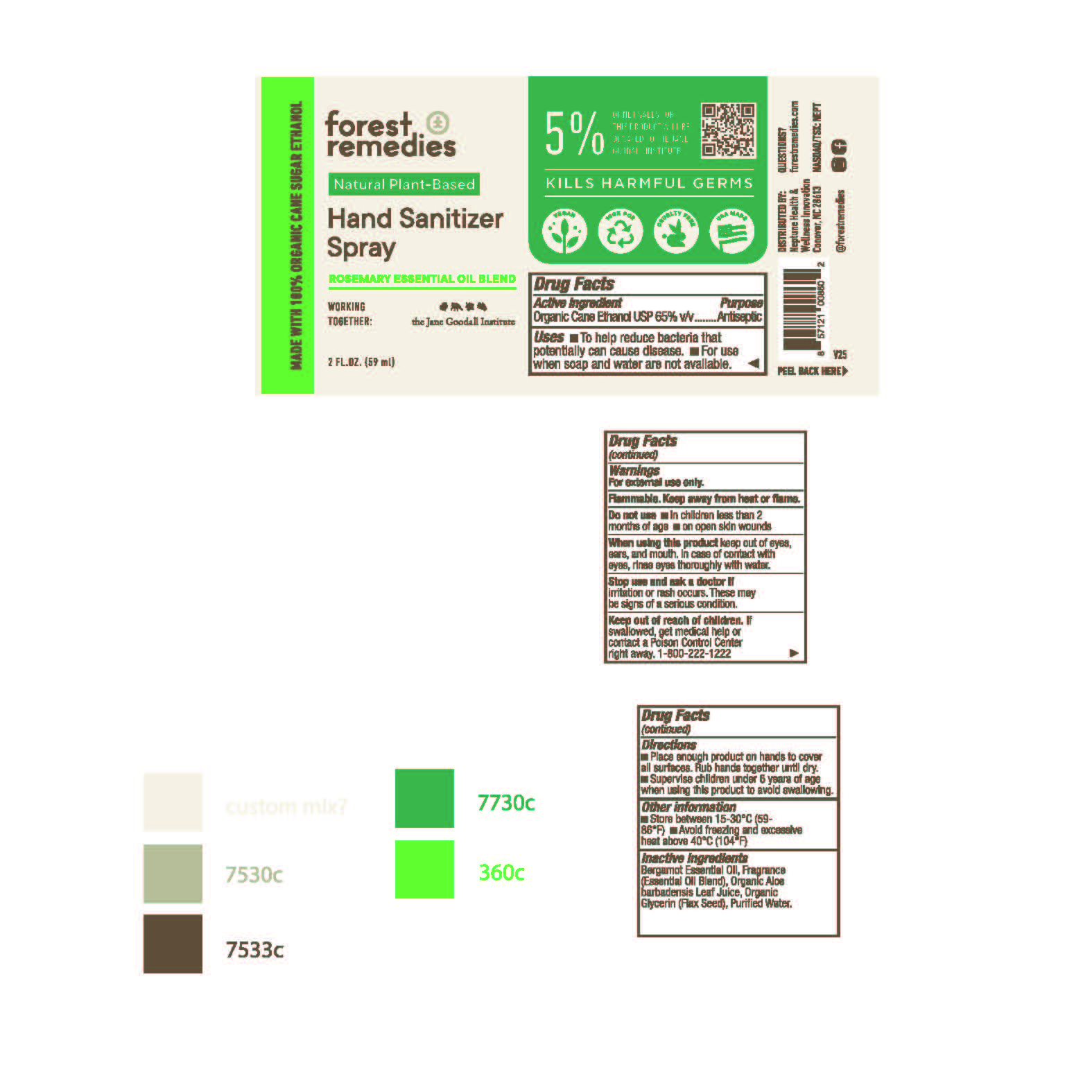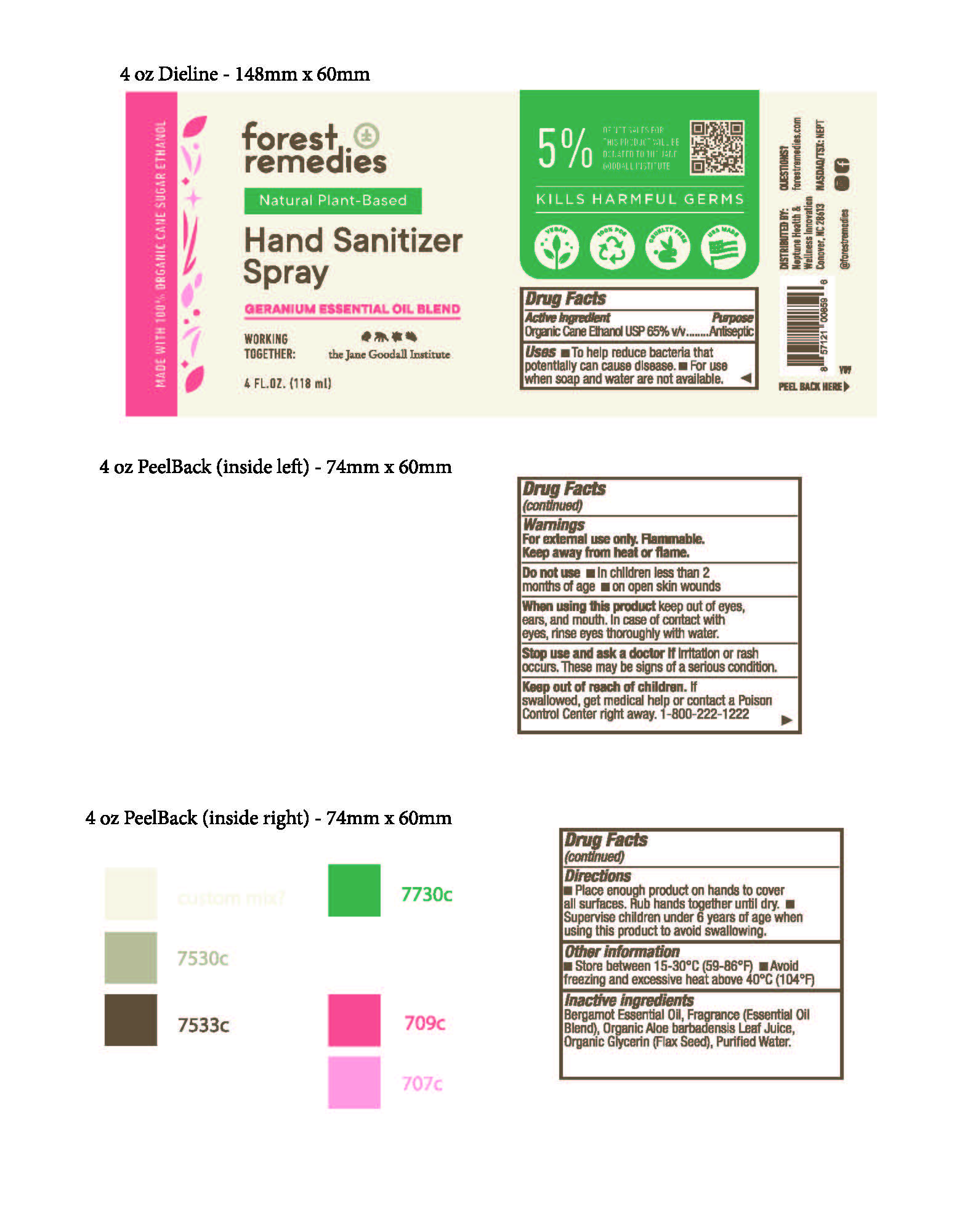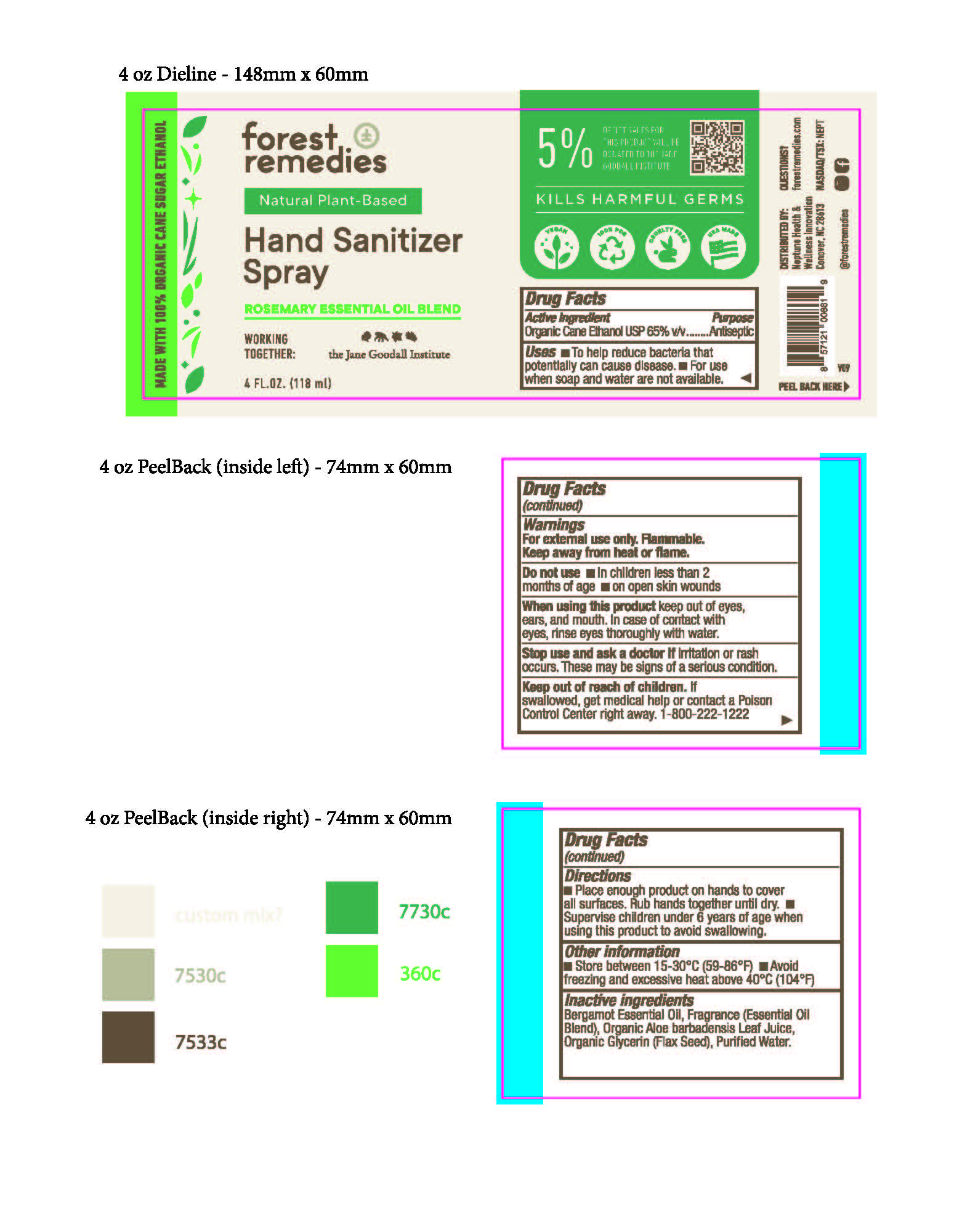 DRUG LABEL: Hand Sanitizer
NDC: 79965-107 | Form: LIQUID
Manufacturer: Neptune Health & Wellness Innovation
Category: otc | Type: HUMAN OTC DRUG LABEL
Date: 20210601

ACTIVE INGREDIENTS: ALCOHOL 65 mL/100 mL
INACTIVE INGREDIENTS: GLYCERIN 3 mL/100 mL; BERGAMOT OIL 0.3 mL/100 mL; WATER 31.68 mL/100 mL; ALOE VERA LEAF 0.02 mL/100 mL

Active Ingredient(s)

Alcohol 65% v/v. Purpose: Antiseptic

Purpose

Antiseptic, Hand Sanitizer

Use

Hand Sanitizer to help reduce bacteria that potentially can cause disease. For use when soap and water are not available.

Warnings

For external use only. Flammable. Keep away from heat or flame

Do not use

- in children less than 2 months of age
- on open skin wounds

When using this product keep out of eyes, ears, and mouth. In case of contact with eyes, rinse eyes thoroughly with water.
Stop use and ask a doctor if irritation or rash occurs. These may be signs of a serious condition.
Keep out of reach of children. If swallowed, get medical help or contact a Poison Control Center right away.

Stop use and ask a doctor if irritation or rash occurs. These may be signs of a serious condition.

Keep out of reach of children. If swallowed, get medical help or contact a Poison Control Center right away.

Directions

- Place enough product on hands to cover all surfaces. Rub hands together until dry.
- Supervise children under 6 years of age when using this product to avoid swallowing.

Other information

- Store between 15-30C (59-86F)
- Avoid freezing and excessive heat above 40C (104F)

Inactive ingredients

Bergamot Essential Oil, Fragrance (Essential Oil Blend), Organic Aloe barbadensis Leaf Juice, Organic Glycerin (Flax Seed), Purified Water.

Package Label - Principal Display Panel

2 fl. oz. (60 mL) NDC: 79965-007-00

4 fl. oz. (120 mL) NDC: 79965-007-01

2 fl. oz. (60 mL) NDC: 79965-107-00

4 fl. oz. (120 mL) NDC: 79965-107-01